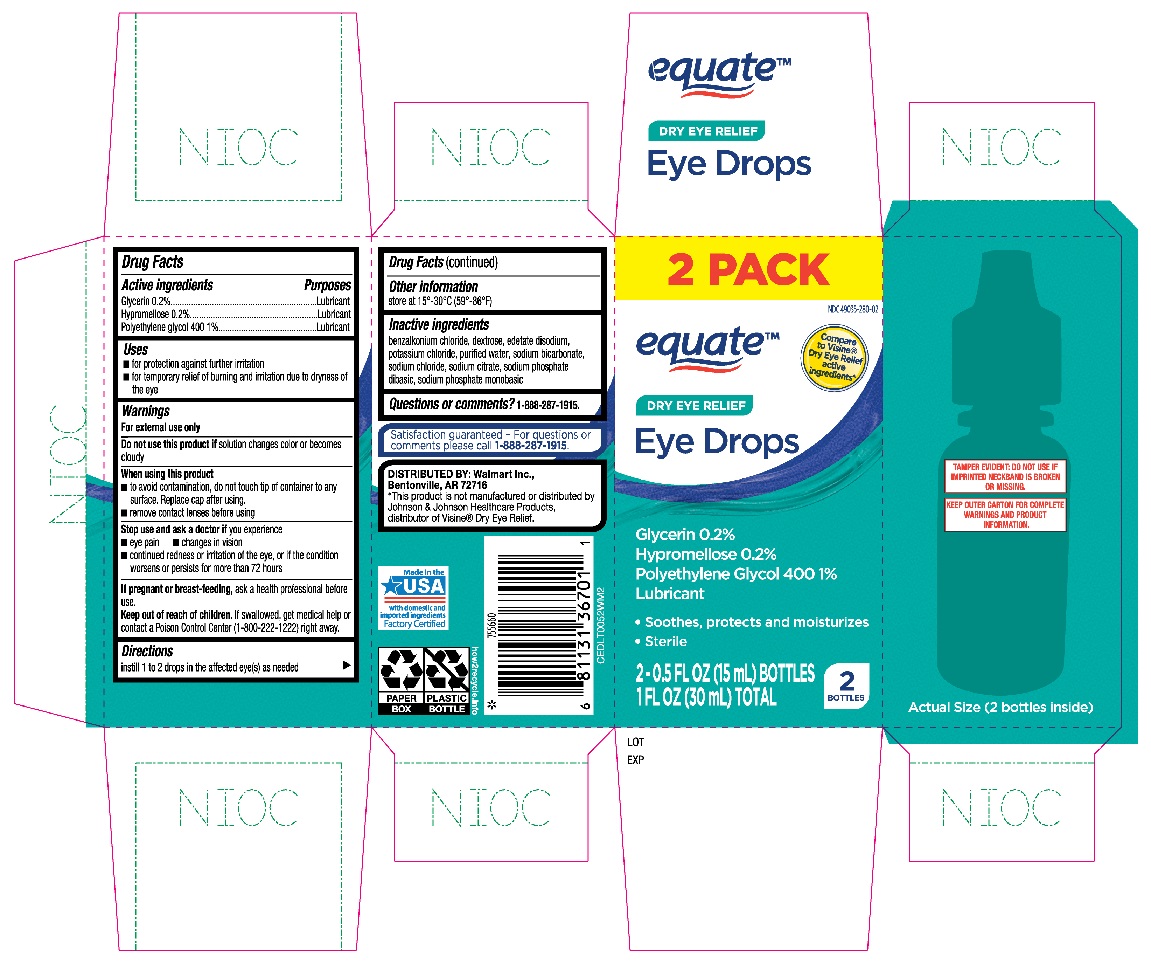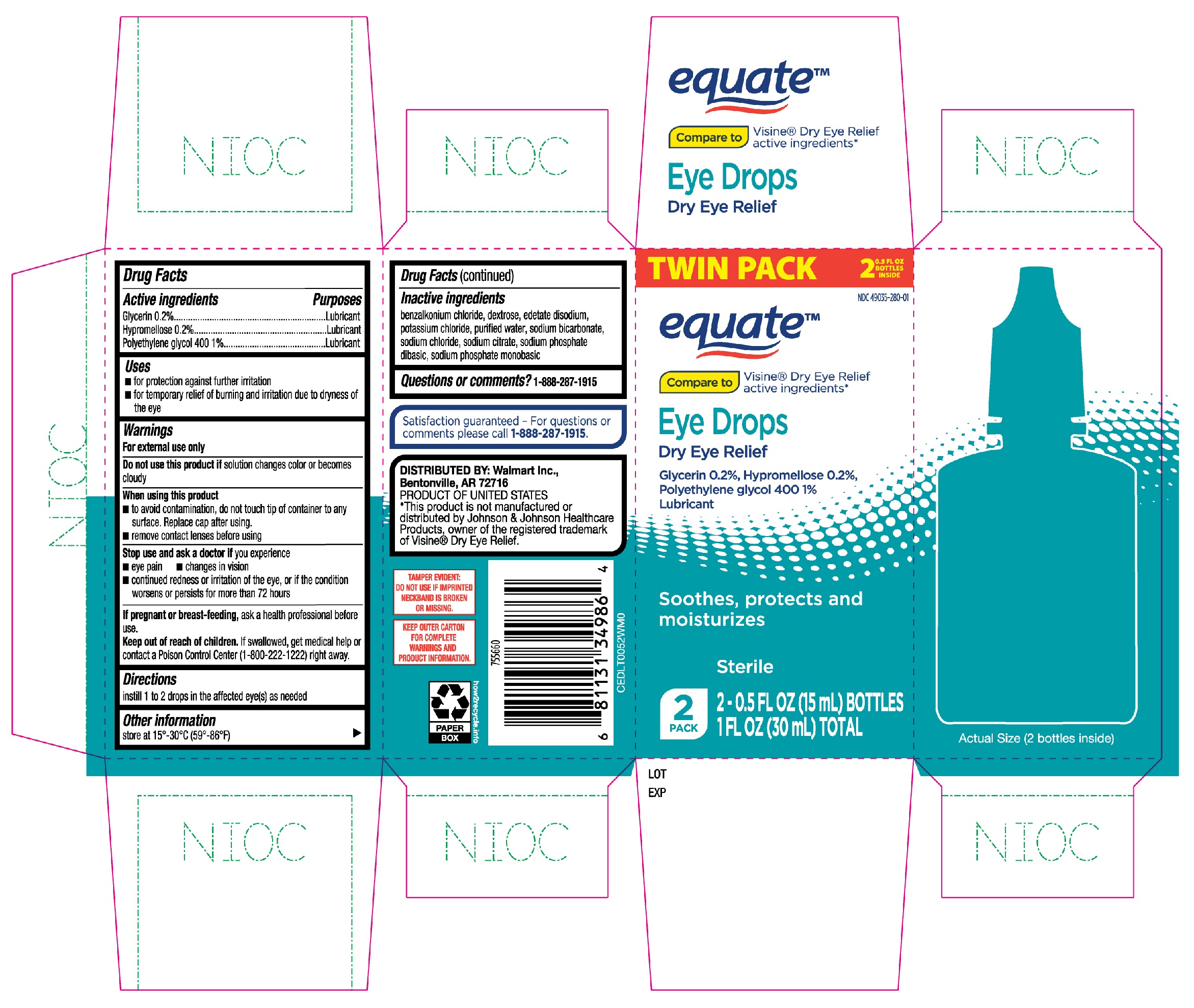 DRUG LABEL: Equate Eye Drops Dry Eye Relief
NDC: 49035-280 | Form: SOLUTION/ DROPS
Manufacturer: Wal-Mart Stores, Inc.
Category: otc | Type: HUMAN OTC DRUG LABEL
Date: 20231223

ACTIVE INGREDIENTS: GLYCERIN 0.2 g/100 mL; HYPROMELLOSE, UNSPECIFIED 0.2 g/100 mL; POLYETHYLENE GLYCOL 400 1 g/100 mL
INACTIVE INGREDIENTS: SODIUM PHOSPHATE, MONOBASIC, ANHYDROUS; POTASSIUM CHLORIDE; SODIUM BICARBONATE; SODIUM PHOSPHATE DIBASIC DIHYDRATE; BENZALKONIUM CHLORIDE; DEXTROSE; EDETATE DISODIUM; WATER; SODIUM CHLORIDE; SODIUM CITRATE

Equate Dry Eye Relief Eye Drops 15mL twin pk (PLD)

Active ingredients

Glycerin 0.2%

Hypromellose 0.2%

Polyethylene glycol 400 1%

Purposes

Lubricant

Lubricant

Lubricant

Uses

- for protection against further irritation
- for temporary relief of burning and irritation due to dryness of the eye

Warnings

For external use only

Do not use this product if

solution changes color or becomes cloudy

When using this product

- to avoid contamination, do not touch tip of container to any surface. Replace cap after using.
- remove contact lenses before using

Stop use and ask a doctor if you experience

- eye pain
- changes in vision
- continued redness or irritation of the eye, or if the condition worsens or persists for more than 72 hours

If pregnant or breast-feeding,

ask a health professional before use.

Keep out of reach of children.

If swallowed, get medical help or contact a Poison Control Center (1-800-222-1222) right away.

Directions

instill 1 to 2 drops in the affected eye(s) as needed

Other information

store at 15°-30°C (59°-86°F)

Inactive ingredients

benzalkonium chloride, dextrose, edetate disodium, potassium chloride, purified water, sodium bicarbonate, sodium chloride, sodium citrate, sodium phosphate dibasic, sodium phosphate monobasic

Questions or comments?

1-888-287-1915